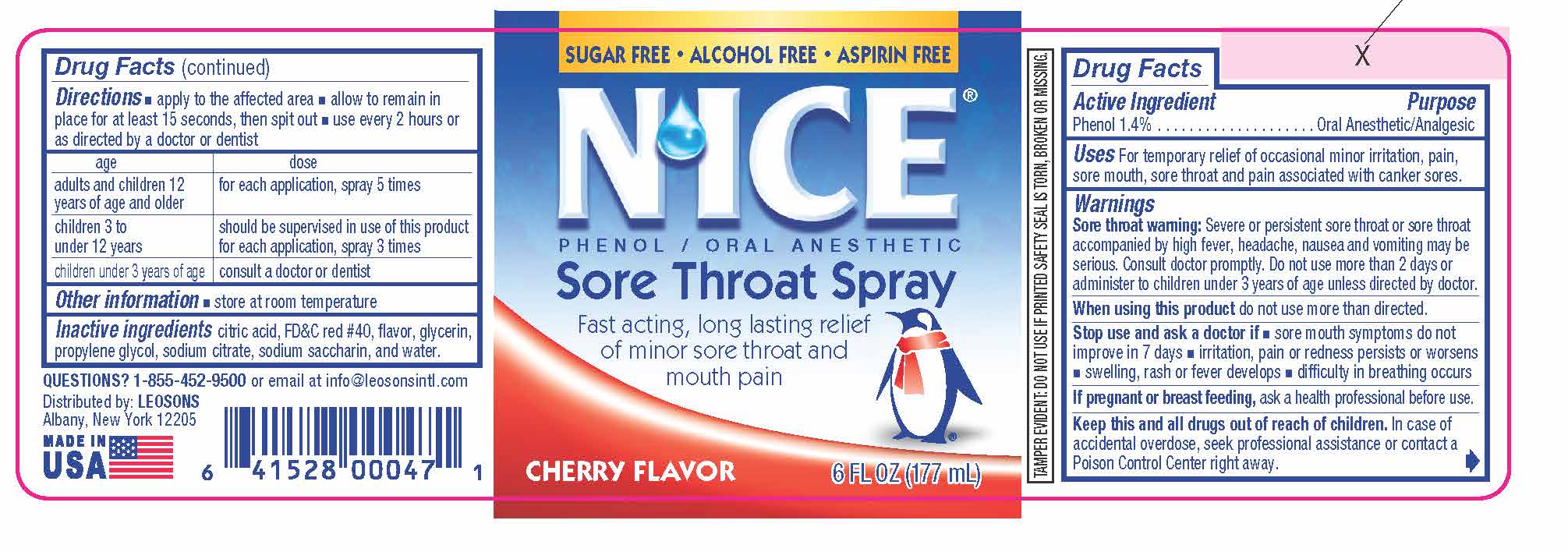 DRUG LABEL: NICE SORE THROAT Cherry
NDC: 69626-0047 | Form: SPRAY
Manufacturer: Leosons Overseas Corp
Category: otc | Type: HUMAN OTC DRUG LABEL
Date: 20241115

ACTIVE INGREDIENTS: PHENOL 1.4 g/100 mL
INACTIVE INGREDIENTS: SACCHARIN SODIUM; CITRIC ACID MONOHYDRATE; FD&C RED NO. 40; GLYCERIN; SODIUM CITRATE; WATER; PROPYLENE GLYCOL

NICE Sore Throat Cherry

Active Ingredients & Purposes

PURPOSE

Active Ingredients | Purposes
Phenol 1.4% | Oral Anesthetic/ Analgesic

Uses

For temporary relief of occasional minor irritation, pain, sore mouth, sore throat and pain associated with canker sores.

Warnings

Sore throat warning:Severe or persistent sore throat or sore throat accompanied by high fever, headache, nausea and vomiting may be serious. Consult doctor promptly. Do not use more than 2 days or administer to children under 3 years of age unless directed by doctor.

WHEN USING

When using this productdo not use more than directed.

Stop use and ask a doctor if

- sore mouth symptoms do not improve in 7 days
- irritation, pain or redness persists or worsens
- swelling, rash or fever develops
- difficulty in breathing occurs

If pregnant or breast feeding,

- ask a health professional before use.

Keep this and all drugs out of reach of children.

In case of accidental overdose, seek professional assistance or contact a Poison Control Center right away.

Directions

- apply to the affected area
- allow to remain in place for at least 15 seconds, then spit out
- use every 2 hours or as directed by a doctor or dentist

age | dose
adults and children 12 years of age and older | for each application, spray 5 times
children 3 to under 12 years | should be supervised in use of this product;; for each application, spray 3 times
children under 3 years of age | consult a doctor or dentist

Other Information

- store at room temperature

TAMPER EVIDENT:DO NOT USE IF PRINTED SAFETY SEAL IS TORN, BROKEN OR MISSING.

Inactive Ingredients

citric acid, FD&C red #40, flavor, glycerin, propylene glycol, sodium citrate, sodium saccharin, and water.

Questions?

1-855-452-9500or email at info@leosonsintl.com

Distributed by:

LEOSONS
Albany, New York 12205

MADE IN THE USA

Principal Display Panel

- Sugar Free
- Alcohol Free
- Aspirin Free

N'ICE®

PHENOL/ ORAL ANESTHETIC

Sore Throat Spray

Fast acting, long lasting relief of minor sore throat and mouth pain

Cherry Flavor

6 FL OZ (177 mL)